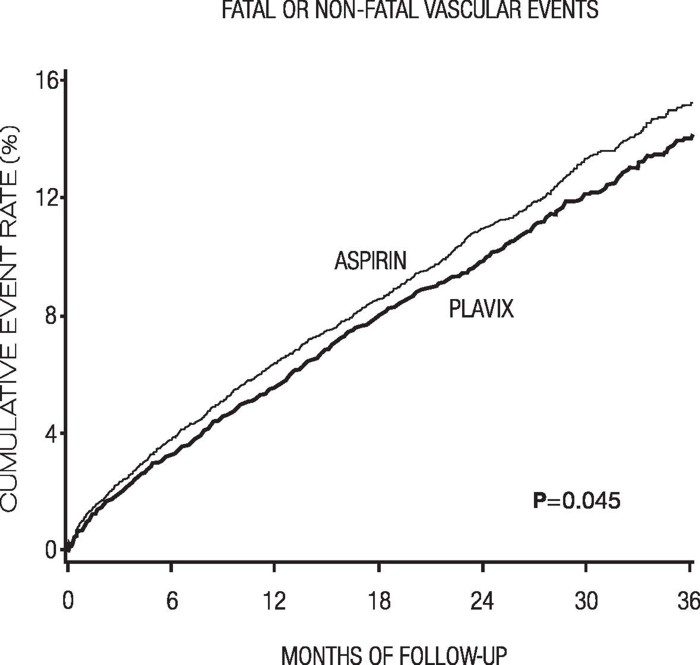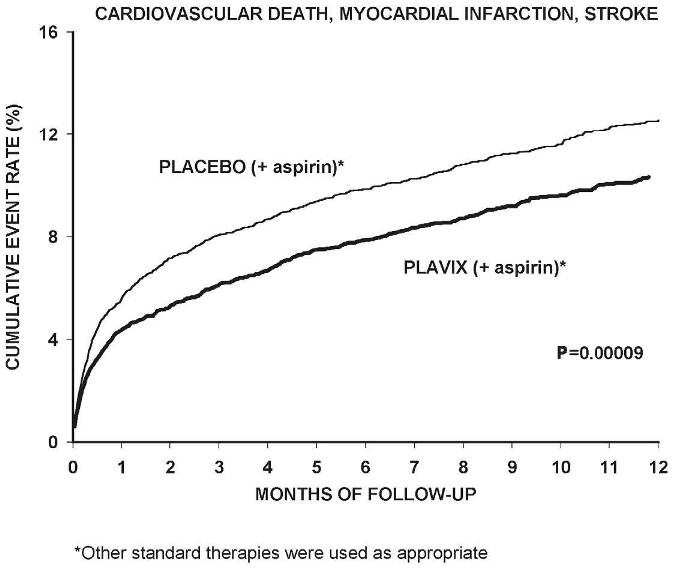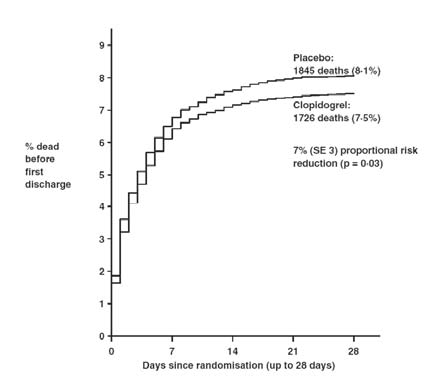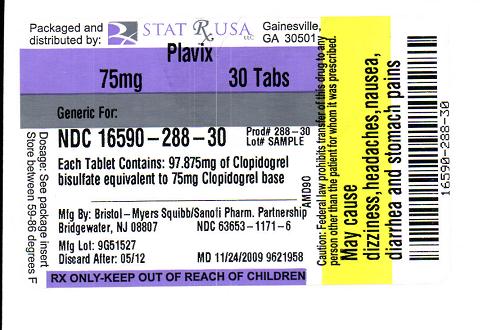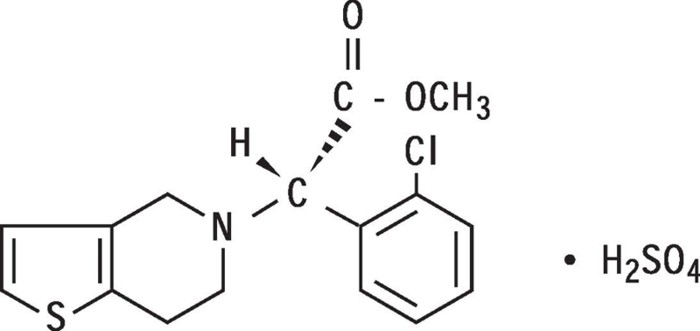 DRUG LABEL: PLAVIX
NDC: 16590-288 | Form: TABLET, FILM COATED
Manufacturer: STAT RX USA LLC
Category: prescription | Type: HUMAN PRESCRIPTION DRUG LABEL
Date: 20091124

ACTIVE INGREDIENTS: CLOPIDOGREL BISULFATE 75 mg/1 1

DESCRIPTION

PLAVIX (clopidogrel bisulfate) is an inhibitor of ADP-induced platelet aggregation acting by direct inhibition of adenosine diphosphate (ADP) binding to its receptor and of the subsequent ADP-mediated activation of the glycoprotein GPIIb/IIIa complex. Chemically it is methyl (+)-(S)-α-(2-chlorophenyl)-6,7-dihydrothieno[3,2-c]pyridine-5(4H)-acetate sulfate (1:1). The empirical formula of clopidogrel bisulfate is C16H16ClNO2S•H2SO4 and its molecular weight is 419.9.

The structural formula is as follows:

Clopidogrel bisulfate is a white to off-white powder. It is practically insoluble in water at neutral pH but freely soluble at pH 1. It also dissolves freely in methanol, dissolves sparingly in methylene chloride, and is practically insoluble in ethyl ether. It has a specific optical rotation of about +56°.

PLAVIX for oral administration is provided as either pink, round, biconvex, debossed, film-coated tablets containing 97.875 mg of clopidogrel bisulfate which is the molar equivalent of 75 mg of clopidogrel base or pink, oblong, debossed film-coated tablets containing 391.5 mg of clopidogrel bisulfate which is the molar equivalent of 300 mg of clopidogrel base.

Each tablet contains hydrogenated castor oil, hydroxypropylcellulose, mannitol, microcrystalline cellulose and polyethylene glycol 6000 as inactive ingredients. The pink film coating contains ferric oxide, hypromellose 2910, lactose monohydrate, titanium dioxide and triacetin. The tablets are polished with Carnauba wax.

CLINICAL PHARMACOLOGY

CLINICAL PHARMACOLOGYMechanism of Action and Pharmacodynamic Properties

Clopidogrel is a prodrug, one of whose metabolites is an inhibitor of platelet aggregation. A variety of drugs that inhibit platelet function have been shown to decrease morbid events in people with established cardiovascular atherosclerotic disease as evidenced by stroke or transient ischemic attacks, myocardial infarction, unstable angina or the need for vascular bypass or angioplasty. This indicates that platelets participate in the initiation and/or evolution of these events and that inhibiting platelet function can reduce the event rate.

Clopidogrel must be metabolized by CYP450 enzymes to produce the active metabolite that inhibits platelet aggregation. The active metabolite of clopidogrel selectively inhibits the binding of adenosine diphosphate (ADP) to its platelet P2Y12 receptor and the subsequent ADP-mediated activation of the glycoprotein GPIIb/IIIa complex, thereby inhibiting platelet aggregation. This action is irreversible. Consequently, platelets exposed to clopidogrel's active metabolite are affected for the remainder of their lifespan (about 7 to 10 days). Platelet aggregation induced by agonists other than ADP is also inhibited by blocking the amplification of platelet activation by released ADP.

Because the active metabolite is formed by CYP450 enzymes, some of which are polymorphic or subject to inhibition by other drugs, not all patients will have adequate platelet inhibition.

Dose dependent inhibition of platelet aggregation can be seen 2 hours after single oral doses of PLAVIX. Repeated doses of 75 mg PLAVIX per day inhibit ADP-induced platelet aggregation on the first day, and inhibition reaches steady state between Day 3 and Day 7. At steady state, the average inhibition level observed with a dose of 75 mg PLAVIX per day was between 40% and 60%. Platelet aggregation and bleeding time gradually return to baseline values after treatment is discontinued, generally in about 5 days.

Pharmacokinetics Absorption

After single and repeated oral doses of 75 mg per day, clopidogrel is rapidly absorbed. Mean peak plasma levels of unchanged clopidogrel (approximately 2.2-2.5 ng/mL after a single 75-mg oral dose) occurred approximately 45 minutes after dosing. Absorption is at least 50%, based on urinary excretion of clopidogrel metabolites.

Effect of Food

The effect of food on the bioavailability of the parent compound or active metabolite is currently not known.

Distribution

Clopidogrel and the main circulating inactive metabolite bind reversibly in vitro to human plasma proteins (98% and 94%, respectively). The binding is nonsaturable in vitro up to a concentration of 100 mcg/mL.

Metabolism

Clopidogrel is extensively metabolized by the liver. In vitro and in vivo, clopidogrel is metabolized according to two main metabolic pathways: one mediated by esterases and leading to hydrolysis into its inactive carboxylic acid derivative (85% of circulating metabolites), and one mediated by multiple cytochromes P450. Cytochromes first oxidize clopidogrel to a 2-oxo-clopidogrel intermediate metabolite. Subsequent metabolism of the 2-oxo-clopidogrel intermediate metabolite results in formation of the active metabolite, a thiol derivative of clopidogrel. In vitro, this metabolic pathway is mediated by CYP3A4, CYP2C19, CYP1A2 and CYP2B6. The active thiol metabolite, which has been isolated in vitro, binds rapidly and irreversibly to platelet receptors, thus inhibiting platelet aggregation.

Elimination

Following an oral dose of ^14C-labeled clopidogrel in humans, approximately 50% of total radioactivity was excreted in urine and approximately 46% in feces over the 5 days post-dosing. After a single, oral dose of 75 mg, clopidogrel has a half-life of approximately 6 hours. The elimination half-life of the inactive acid metabolite was 8 hours after single and repeated administration. Covalent binding to platelets accounted for 2% of radiolabel with a half-life of 11 days. In plasma and urine, the glucuronide of the carboxylic acid derivative is also observed.

Pharmacogenetics

Several polymorphic CYP450 enzymes activate clopidogrel. CYP2C19 is involved in the formation of both the active metabolite and the 2-oxo-clopidogrel intermediate metabolite. Clopidogrel active metabolite pharmacokinetics and antiplatelet effects, as measured by ex vivo platelet aggregation assays, differ according to CYP2C19 genotype. The CYP2C19*1 allele corresponds to fully functional metabolism while the CYP2C19*2 and CYP2C19*3 alleles correspond to reduced metabolism. The CYP2C19*2 and CYP2C19*3 alleles account for 85% of reduced function alleles in whites and 99% in Asians. Other alleles associated with reduced metabolism include CYP2C19*4, *5, *6, *7, and *8, but these are less frequent in the general population. Published frequencies for the common CYP2C19 phenotypes and genotypes are listed in the table below.

To date, the impact of CYP2C19 genotype on the pharmacokinetics of clopidogrel's active metabolite has been evaluated in 227 subjects from 7 reported studies. Reduced CYP2C19 metabolism in intermediate and poor metabolizers decreased the Cmax and AUC of the active metabolite by 30-50% following 300- or 600 mg loading doses and 75 mg maintenance doses. Lower active metabolite exposure results in less platelet inhibition or higher residual platelet reactivity. To date, diminished antiplatelet responses to clopidogrel have been described for intermediate and poor metabolizers in 21 reported studies involving 4,520 subjects. The relative difference in antiplatelet response between genotype groups varies across studies depending on the method used to evaluate response, but is typically greater than 30%.

The association between CYP2C19 genotype and clopidogrel treatment outcome was evaluated in 2 post-hoc clinical trial analyses (substudies of CLARITY-TIMI 281 [n=465] and TRITON-TIMI 382 [n=1,477]) and 5 cohort studies (total n=6,489). In CLARITY-TIMI 28 and one of the cohort studies (n=765; Trenk3), cardiovascular event rates did not differ significantly by genotype. In TRITON-TIMI 38 and 3 of the cohort studies (n= 3,516; Collet,4 Sibbing,5 Giusti6), patients with an impaired metabolizer status (intermediate and poor combined) had a higher rate of cardiovascular events (death, myocardial infarction, and stroke) or stent thrombosis compared to extensive metabolizers. In the fifth cohort study (n=2,208; Simon7), the increased event rate was observed only in poor metabolizers.

Pharmacogenetic testing can identify genotypes associated with variability in CYP2C19 activity.

There may be genetic variants of other CYP450 enzymes with effects on the ability to form clopidogrel's active metabolite.

1Mega JL, Thakuria JV, Cannon CP, Sabatine MS. Sequence variations in CYP metabolism genes and cardiovascular outcomes following treatment with clopidogrel: insights from the CLARITY-TIMI 28 genomic study. 2008; ACC Meeting Abstract 2Mega et al. Cytochrome P-450 polymorphisms and response to clopidogrel. N Engl J Med 2009; 360:354-62 3Trenk et al. Cytochrome P450 2C19 681G>A polymorphism and high on-clopidogrel platelet reactivity associated with adverse 1-year clinical outcome of elective percutaneous coronary intervention with drug-eluting or bare-metal stents. J Am Coll Cardiol 2008; 51, 20: 1952 4Collet JP et al. Cytochrome P450 2C19 polymorphism in young patients treated with clopidogrel after myocardial infarction: a cohort study. The Lancet 2009; 373: 309-317 5Sibbing D et al. Cytochrome P450 2C19 loss-of-function polymorphism and stent thrombosis following percutaneous coronary intervention. Eur Heart J 2009:1-7 6Giusti et al. Relation of cytochrome P450 2C19 loss-of-function polymorphism to occurrence of drug-eluting coronary stent thrombosis. Am J Cardiol 2009; 103:806–811 7Simon et al. Genetic determinants of response to clopidogrel and cardiovascular events. N Engl J Med 2009; 360(4):363-75 Special Populations

The pharmacokinetics of clopidogrel's active metabolite is not known in these special populations.

Geriatric Patients

In elderly (≥75 years) volunteers compared to young healthy volunteers, there were no differences in platelet aggregation and bleeding time. No dosage adjustment is needed for the elderly.

Renally-Impaired Patients

After repeated doses of 75 mg PLAVIX per day in patients with severe renal impairment (creatinine clearance from 5 to 15 mL/min), inhibition of ADP-induced platelet aggregation was lower (25%) than that observed in healthy volunteers, however, the prolongation of bleeding time was similar to healthy volunteers receiving 75 mg of PLAVIX per day.

Hepatically-Impaired Patients

After repeated doses of 75 mg PLAVIX per day for 10 days in patients with severe hepatic impairment, inhibition of ADP-induced platelet aggregation was similar to that observed in healthy subjects. The mean bleeding time prolongation was also similar in the two groups.

Gender

In a small study comparing men and women, less inhibition of ADP-induced platelet aggregation was observed in women, but there was no difference in prolongation of bleeding time. In the large, controlled clinical study (Clopidogrel vs. Aspirin in Patients at Risk of Ischemic Events; CAPRIE), the incidence of clinical outcome events, other adverse clinical events, and abnormal clinical laboratory parameters was similar in men and women.

Race

The prevalence of CYP2C19 alleles that result in intermediate and poor CYP2C19 metabolism differs according to race/ethnicity (see CLINICAL PHARMACOLOGY: Pharmacogenetics).

CLINICAL STUDIES

The clinical evidence for the efficacy of PLAVIX is derived from four double-blind trials involving 81,090 patients: the CAPRIE study (Clopidogrel vs. Aspirin in Patients at Risk of Ischemic Events), a comparison of PLAVIX to aspirin, and the CURE (Clopidogrel in Unstable Angina to Prevent Recurrent Ischemic Events), the COMMIT/CCS-2 (Clopidogrel and Metoprolol in Myocardial Infarction Trial / Second Chinese Cardiac Study) studies comparing PLAVIX to placebo, both given in combination with aspirin and other standard therapy and CLARITY-TIMI 28 (Clopidogrel as Adjunctive Reperfusion Therapy – Thrombolysis in Myocardial Infarction).

Recent Myocardial Infarction (MI), Recent Stroke or Established Peripheral Arterial Disease

The CAPRIE trial was a 19,185-patient, 304-center, international, randomized, double-blind, parallel-group study comparing PLAVIX (75 mg daily) to aspirin (325 mg daily). The patients randomized had: 1) recent histories of myocardial infarction (within 35 days); 2) recent histories of ischemic stroke (within 6 months) with at least a week of residual neurological signs; or 3) objectively established peripheral arterial disease. Patients received randomized treatment for an average of 1.6 years (maximum of 3 years).

The trial's primary outcome was the time to first occurrence of new ischemic stroke (fatal or not), new myocardial infarction (fatal or not), or other vascular death. Deaths not easily attributable to nonvascular causes were all classified as vascular.

As shown in the table, PLAVIX (clopidogrel bisulfate) was associated with a lower incidence of outcome events of every kind. The overall risk reduction (9.8% vs. 10.6%) was 8.7%, P=0.045. Similar results were obtained when all-cause mortality and all-cause strokes were counted instead of vascular mortality and ischemic strokes (risk reduction 6.9%). In patients who survived an on-study stroke or myocardial infarction, the incidence of subsequent events was again lower in the PLAVIX group.

The curves showing the overall event rate are shown in Figure 1. The event curves separated early and continued to diverge over the 3-year follow-up period.

CHART

Although the statistical significance favoring PLAVIX over aspirin was marginal (P=0.045), and represents the result of a single trial that has not been replicated, the comparator drug, aspirin, is itself effective (vs. placebo) in reducing cardiovascular events in patients with recent myocardial infarction or stroke. Thus, the difference between PLAVIX and placebo, although not measured directly, is substantial.

The CAPRIE trial included a population that was randomized on the basis of 3 entry criteria. The efficacy of PLAVIX relative to aspirin was heterogeneous across these randomized subgroups (P=0.043). It is not clear whether this difference is real or a chance occurrence. Although the CAPRIE trial was not designed to evaluate the relative benefit of PLAVIX over aspirin in the individual patient subgroups, the benefit appeared to be strongest in patients who were enrolled because of peripheral vascular disease (especially those who also had a history of myocardial infarction) and weaker in stroke patients. In patients who were enrolled in the trial on the sole basis of a recent myocardial infarction, PLAVIX was not numerically superior to aspirin.

In the meta-analyses of studies of aspirin vs. placebo in patients similar to those in CAPRIE, aspirin was associated with a reduced incidence of thrombotic events. There was a suggestion of heterogeneity in these studies too, with the effect strongest in patients with a history of myocardial infarction, weaker in patients with a history of stroke, and not discernible in patients with a history of peripheral vascular disease. With respect to the inferred comparison of PLAVIX to placebo, there is no indication of heterogeneity.

Acute Coronary Syndrome

The CURE study included 12,562 patients with acute coronary syndrome without ST segment elevation (unstable angina or non-Q-wave myocardial infarction) and presenting within 24 hours of onset of the most recent episode of chest pain or symptoms consistent with ischemia. Patients were required to have either ECG changes compatible with new ischemia (without ST segment elevation) or elevated cardiac enzymes or troponin I or T to at least twice the upper limit of normal. The patient population was largely Caucasian (82%) and included 38% women, and 52% patients ≥65 years of age.

Patients were randomized to receive PLAVIX (300 mg loading dose followed by 75 mg/day) or placebo, and were treated for up to one year. Patients also received aspirin (75–325 mg once daily) and other standard therapies such as heparin. The use of GPIIb/IIIa inhibitors was not permitted for three days prior to randomization.

The number of patients experiencing the primary outcome (CV death, MI, or stroke) was 582 (9.30%) in the PLAVIX-treated group and 719 (11.41%) in the placebo-treated group, a 20% relative risk reduction (95% CI of 10%–28%; p=0.00009) for the PLAVIX-treated group (see Table 3).

At the end of 12 months, the number of patients experiencing the co-primary outcome (CV death, MI, stroke or refractory ischemia) was 1035 (16.54%) in the PLAVIX-treated group and 1187 (18.83%) in the placebo-treated group, a 14% relative risk reduction (95% CI of 6%–21%, p=0.0005) for the PLAVIX-treated group (see Table 3).

In the PLAVIX-treated group, each component of the two primary endpoints (CV death, MI, stroke, refractory ischemia) occurred less frequently than in the placebo-treated group.

The benefits of PLAVIX (clopidogrel bisulfate) were maintained throughout the course of the trial (up to 12 months).

CHART 2

In CURE, the use of PLAVIX was associated with a lower incidence of CV death, MI or stroke in patient populations with different characteristics, as shown in Figure 3. The benefits associated with PLAVIX were independent of the use of other acute and long-term cardiovascular therapies, including heparin/LMWH (low molecular weight heparin), IV glycoprotein IIb/IIIa (GPIIb/IIIa) inhibitors, lipid-lowering drugs, beta-blockers, and ACE-inhibitors. The efficacy of PLAVIX was observed independently of the dose of aspirin (75–325 mg once daily). The use of oral anticoagulants, non-study anti-platelet drugs and chronic NSAIDs was not allowed in CURE.

The use of PLAVIX in CURE was associated with a decrease in the use of thrombolytic therapy (71 patients [1.1%] in the PLAVIX group, 126 patients [2.0%] in the placebo group; relative risk reduction of 43%, P=0.0001), and GPIIb/IIIa inhibitors (369 patients [5.9%] in the PLAVIX group, 454 patients [7.2%] in the placebo group, relative risk reduction of 18%, P=0.003). The use of PLAVIX in CURE did not impact the number of patients treated with CABG or PCI (with or without stenting), (2253 patients [36.0%] in the PLAVIX group, 2324 patients [36.9%] in the placebo group; relative risk reduction of 4.0%, P=0.1658).

In patients with ST-segment elevation acute myocardial infarction, safety and efficacy of clopidogrel have been evaluated in two randomized, placebo-controlled, double-blind studies, COMMIT- a large outcome study conducted in China - and CLARITY- a supportive study of a surrogate endpoint conducted internationally.

The randomized, double-blind, placebo-controlled, 2×2 factorial design COMMIT trial included 45,852 patients presenting within 24 hours of the onset of the symptoms of suspected myocardial infarction with supporting ECG abnormalities (i.e., ST elevation, ST depression or left bundle-branch block). Patients were randomized to receive PLAVIX (75 mg/day) or placebo, in combination with aspirin (162 mg/day), for 28 days or until hospital discharge whichever came first.

The co-primary endpoints were death from any cause and the first occurrence of re-infarction, stroke or death.

The patient population included 28% women, 58% patients ≥60 years (26% patients ≥70 years) and 55% patients who received thrombolytics, 68% received ace-inhibitors, and only 3% had percutaneous coronary intervention (PCI).

As shown in Table 4 and Figures 4 and 5 below, PLAVIX significantly reduced the relative risk of death from any cause by 7% (p = 0.029), and the relative risk of the combination of re-infarction, stroke or death by 9% (p = 0.002).

CHART 3

The effect of PLAVIX did not differ significantly in various pre-specified subgroups as shown in Figure 6. Additionally, the effect was similar in non-prespecified subgroups including those based on infarct location, Killip class or prior MI history (see Figure 7). Such subgroup analyses should be interpreted very cautiously.

The randomized, double-blind, placebo-controlled CLARITY trial included 3,491 patients, 5% U.S., presenting within 12 hours of the onset of a ST elevation myocardial infarction and planned for thrombolytic therapy. Patients were randomized to receive PLAVIX (300-mg loading dose, followed by 75 mg/day) or placebo until angiography, discharge, or Day 8. Patients also received aspirin (150 to 325 mg as a loading dose, followed by 75 to 162 mg/day), a fibrinolytic agent and, when appropriate, heparin for 48 hours. The patients were followed for 30 days.

The primary endpoint was the occurrence of the composite of an occluded infarct-related artery (defined as TIMI Flow Grade 0 or 1) on the predischarge angiogram, or death or recurrent myocardial infarction by the time of the start of coronary angiography.

The patient population was mostly Caucasian (89.5%) and included 19.7% women and 29.2% patients ≥65 years. A total of 99.7% of patients received fibrinolytics (fibrin specific: 68.7%, non-fibrin specific: 31.1%), 89.5% heparin, 78.7% beta-blockers, 54.7% ACE inhibitors and 63% statins.

The number of patients who reached the primary endpoint was 262 (15.0%) in the PLAVIX-treated group and 377 (21.7%) in the placebo group, but most of the events related to the surrogate endpoint of vessel patency.

INDICATIONS AND USAGE

PLAVIX (clopidogrel bisulfate) is indicated for the reduction of atherothrombotic events as follows:

- Recent MI, Recent Stroke or Established Peripheral Arterial Disease
  For patients with a history of recent myocardial infarction (MI), recent stroke, or established peripheral arterial disease, PLAVIX has been shown to reduce the rate of a combined endpoint of new ischemic stroke (fatal or not), new MI (fatal or not), and other vascular death.
- Acute Coronary Syndrome- For patients with non-ST-segment elevation acute coronary syndrome (unstable angina/non-Q-wave MI) including patients who are to be managed medically and those who are to be managed with percutaneous coronary intervention (with or without stent) or CABG, PLAVIX has been shown to decrease the rate of a combined endpoint of cardiovascular death, MI, or stroke as well as the rate of a combined endpoint of cardiovascular death, MI, stroke, or refractory ischemia. - For patients with ST-segment elevation acute myocardial infarction, PLAVIX has been shown to reduce the rate of death from any cause and the rate of a combined endpoint of death, re-infarction or stroke. This benefit is not known to pertain to patients who receive primary angioplasty

CONTRAINDICATIONS

The use of PLAVIX is contraindicated in the following conditions:

Hypersensitivity to the drug substance or any component of the product. Active pathological bleeding such as peptic ulcer or intracranial hemorrhage.

WARNINGS AND PRECAUTIONS

WARNINGSReduced effectiveness due to impaired CYP2C19 function

The inhibition of platelet aggregation by clopidogrel is entirely due to an active metabolite. Clopidogrel is metabolized to this active metabolite in part by CYP2C19. This metabolism can be impaired by genetic variations in CYP2C19 and by concomitant medications that interfere with CYP2C19. Avoid use of PLAVIX in patients with impaired CYP2C19 function due to known genetic variation or due to drugs that inhibit CYP2C19 activity.

Genetic variations

Patients with genetically reduced CYP2C19 function have diminished antiplatelet responses and generally exhibit higher cardiovascular event rates following myocardial infarction than do patients with normal CYP2C19 function (see CLINICAL PHARMACOLOGY: Pharmacogenetics).

Drug interactions

Co-administration of PLAVIX with omeprazole, a proton pump inhibitor that is an inhibitor of CYP2C19, reduces the pharmacological activity of PLAVIX if given concomitantly or if given 12 hours apart. There is no evidence that other drugs that reduce stomach acid, such as most H2 blockers (except cimetidine, which is a CYP2C19 inhibitor) or antacids interfere with the antiplatelet activity of clopidogrel (see PRECAUTIONS: Drug Interactions).

Thrombotic thrombocytopenic purpura (TTP)

TTP has been reported rarely following use of PLAVIX, sometimes after a short exposure (less than 2 weeks). TTP is a serious condition that can be fatal and requires urgent treatment including plasmapheresis (plasma exchange). It is characterized by thrombocytopenia, microangiopathic hemolytic anemia (schistocytes [fragmented RBCs] seen on peripheral smear), neurological findings, renal dysfunction, and fever. (See ADVERSE REACTIONS.)

PRECAUTIONS

General: PLAVIX prolongs the bleeding time and therefore should be used with caution in patients who may be at risk of increased bleeding from trauma, surgery, or other pathological conditions (particularly gastrointestinal and intraocular). If a patient is to undergo elective surgery and an antiplatelet effect is not desired, PLAVIX should be discontinued 5 days prior to surgery.

Due to the risk of bleeding and undesirable hematological effects, blood cell count determination and/or other appropriate testing should be promptly considered, whenever such suspected clinical symptoms arise during the course of treatment (see ADVERSE REACTIONS).

In patients with recent TIA or stroke who are at high risk of recurrent ischemic events, the combination of aspirin and PLAVIX has not been shown to be more effective than PLAVIX alone, but the combination has been shown to increase major bleeding.

GI Bleeding: In CAPRIE, PLAVIX was associated with a rate of gastrointestinal bleeding of 2.0%, vs. 2.7% on aspirin. In CURE, the incidence of major gastrointestinal bleeding was 1.3% vs. 0.7% (PLAVIX + aspirin vs. placebo + aspirin, respectively). PLAVIX should be used with caution in patients who have lesions with a propensity to bleed (such as ulcers). Drugs that might induce such lesions should be used with caution in patients taking PLAVIX.

Use in Hepatically-Impaired Patients: Experience is limited in patients with severe hepatic disease, who may have bleeding diatheses. PLAVIX should be used with caution in this population.

Use in Renally-Impaired Patients: Experience is limited in patients with severe renal impairment. PLAVIX should be used with caution in this population.

ADVERSE REACTIONS

PLAVIX has been evaluated for safety in more than 42,000 patients, including over 9,000 patients treated for 1 year or more. The clinically important adverse events observed in CAPRIE, CURE, CLARITY and COMMIT are discussed below.

The overall tolerability of PLAVIX in CAPRIE was similar to that of aspirin regardless of age, gender and race, with an approximately equal incidence (13%) of patients withdrawing from treatment because of adverse reactions.

Hemorrhagic

In CAPRIE patients receiving PLAVIX, gastrointestinal hemorrhage occurred at a rate of 2.0%, and required hospitalization in 0.7%. In patients receiving aspirin, the corresponding rates were 2.7% and 1.1%, respectively. The incidence of intracranial hemorrhage was 0.4% for PLAVIX compared to 0.5% for aspirin.

In CURE, PLAVIX use with aspirin was associated with an increase in bleeding compared to placebo with aspirin (see Table 6). There was an excess in major bleeding in patients receiving PLAVIX plus aspirin compared with placebo plus aspirin, primarily gastrointestinal and at puncture sites. The incidence of intracranial hemorrhage (0.1%), and fatal bleeding (0.2%), were the same in both groups.

The overall incidence of bleeding is described in Table 6 for patients receiving both PLAVIX and aspirin in CURE.

Ninety-two percent (92%) of the patients in the CURE study received heparin/LMWH, and the rate of bleeding in these patients was similar to the overall results.

There was no excess in major bleeds within seven days after coronary bypass graft surgery in patients who stopped therapy more than five days prior to surgery (event rate 4.4% PLAVIX + aspirin; 5.3% placebo + aspirin). In patients who remained on therapy within five days of bypass graft surgery, the event rate was 9.6% for PLAVIX + aspirin, and 6.3% for placebo + aspirin.

In CLARITY, the incidence of major bleeding (defined as intracranial bleeding or bleeding associated with a fall in hemoglobin great than 5 g/dL) was similar between groups (1.3% versus 1.1% in the PLAVIX + aspirin and in the placebo + aspirin groups, respectively). This was consistent across subgroups of patients defined by baseline characteristics, and type of fibrinolytics or heparin therapy. The incidence of fatal bleeding (0.8% versus 0.6% in the PLAVIX + aspirin and in the placebo + aspirin groups, respectively) and intracranial hemorrhage (0.5% versus 0.7%, respectively) was low and similar in both groups.

The overall rate of noncerebral major bleeding or cerebral bleeding in COMMIT was low and similar in both groups as shown in Table 7 below

Adverse events occurring in greater than or equal to 2.5% of patients on PLAVIX in the CAPRIE controlled clinical trial are shown below regardless of relationship to PLAVIX. The median duration of therapy was 20 months, with a maximum of 3 years

No additional clinically relevant events to those observed in CAPRIE with a frequency greater than or equal to 2.5%, have been reported during the CURE and CLARITY controlled studies. COMMIT collected only limited safety data.

Other adverse experiences of potential importance occurring in 1% to 2.5% of patients receiving PLAVIX (clopidogrel bisulfate) in the controlled clinical trials are listed below regardless of relationship to PLAVIX. In general, the incidence of these events was similar to that in patients receiving aspirin (in CAPRIE) or placebo + aspirin (in the other clinical trials).

Autonomic Nervous System Disorders: Syncope, Palpitation. Body as a Whole-general disorders: Asthenia, Fever, Hernia. Cardiovascular disorders: Cardiac failure. Central and peripheral nervous system disorders: Cramps legs, Hypoaesthesia, Neuralgia, Paraesthesia, Vertigo. Gastrointestinal system disorders: Constipation, Vomiting. Heart rate and rhythm disorders: Fibrillation atrial. Liver and biliary system disorders: Hepatic enzymes increased. Metabolic and nutritional disorders: Gout, hyperuricemia, non-protein nitrogen (NPN) increased. Musculo-skeletal system disorders: Arthritis, Arthrosis. Platelet, bleeding and clotting disorders: GI hemorrhage, hematoma, platelets decreased. Psychiatric disorders: Anxiety, Insomnia. Red blood cell disorders: Anemia. Respiratory system disorders: Pneumonia, Sinusitis. Skin and appendage disorders: Eczema, Skin ulceration. Urinary system disorders: Cystitis. Vision disorders: Cataract, Conjunctivitis.

Other potentially serious adverse events which may be of clinical interest but were rarely reported (less than 1%) in patients who received PLAVIX in the controlled clinical trials are listed below regardless of relationship to PLAVIX. In general, the incidence of these events was similar to that in patients receiving aspirin (in CAPRIE) or placebo + aspirin (in the other clinical trials).

Body as a whole: Allergic reaction, necrosis ischemic. Cardiovascular disorders: Edema generalized. Gastrointestinal system disorders: Peptic, gastric or duodenal ulcer, gastritis, gastric ulcer perforated, gastritis hemorrhagic, upper GI ulcer hemorrhagic. Liver and Biliary system disorders: Bilirubinemia, hepatitis infectious, liver fatty. Platelet, bleeding and clotting disorders: hemarthrosis, hematuria, hemoptysis, hemorrhage intracranial, hemorrhage retroperitoneal, hemorrhage of operative wound, ocular hemorrhage, pulmonary hemorrhage, purpura allergic, thrombocytopenia. Red blood cell disorders: Anemia aplastic, anemia hypochromic. Reproductive disorders, female: Menorrhagia. Respiratory system disorders: Hemothorax. Skin and appendage disorders: Bullous eruption, rash erythematous, rash maculopapular, urticaria. Urinary system disorders: Abnormal renal function, acute renal failure. White cell and reticuloendothelial system disorders: Agranulocytosis, granulocytopenia, leukemia, leukopenia, neutropenia.

Postmarketing Experience

The following events have been reported spontaneously from worldwide postmarketing experience:

- Body as a whole:- hypersensitivity reactions, anaphylactoid reactions, serum sickness
- Central and Peripheral Nervous System disorders:- confusion, hallucinations, taste disorders
- Hepato-biliary disorders:- abnormal liver function test, hepatitis (non-infectious), acute liver failure
- Platelet, Bleeding and Clotting disorders:- cases of bleeding with fatal outcome (especially intracranial, gastrointestinal and retroperitoneal hemorrhage) - thrombotic thrombocytopenic purpura (TTP) – some cases with fatal outcome – (see WARNINGS) - agranulocytosis, aplastic anemia/pancytopenia - conjunctival, ocular and retinal bleeding
- Respiratory, thoracic and mediastinal disorders:- bronchospasm, interstitial pneumonitis
- Skin and subcutaneous tissue disorders:- angioedema, erythema multiforme, Stevens-Johnson syndrome, toxic epidermal necrolysis, lichen planus
- Renal and urinary disorders:- glomerulopathy, increased creatinine levels
- Vascular disorders:- vasculitis, hypotension
- Gastrointestinal disorders:- colitis (including ulcerative or lymphocytic colitis), pancreatitis, stomatitis
- Musculoskeletal, connective tissue and bone disorders:- myalgia

OVERDOSAGE

Overdose following clopidogrel administration may lead to prolonged bleeding time and subsequent bleeding complications. A single oral dose of clopidogrel at 1500 or 2000 mg/kg was lethal to mice and to rats and at 3000 mg/kg to baboons. Symptoms of acute toxicity were vomiting (in baboons), prostration, difficult breathing, and gastrointestinal hemorrhage in all species.

Recommendations About Specific Treatment

Based on biological plausibility, platelet transfusion may be appropriate to reverse the pharmacological effects of PLAVIX if quick reversal is required.

DOSAGE AND ADMINISTRATION

DOSAGE AND ADMINISTRATIONRecent MI, Recent Stroke, or Established Peripheral Arterial Disease

The recommended daily dose of PLAVIX is 75 mg once daily.

Acute Coronary Syndrome

For patients with non-ST-segment elevation acute coronary syndrome (unstable angina/non-Q-wave MI), PLAVIX should be initiated with a single 300-mg loading dose and then continued at 75 mg once daily. Aspirin (75 mg-325 mg once daily) should be initiated and continued in combination with PLAVIX. In CURE, most patients with Acute Coronary Syndrome also received heparin acutely (see CLINICAL STUDIES).

For patients with ST-segment elevation acute myocardial infarction, the recommended dose of PLAVIX is 75 mg once daily, administered in combination with aspirin, with or without thrombolytics. PLAVIX may be initiated with or without a loading dose (300 mg was used in CLARITY; see CLINICAL STUDIES).

Pharmacogenetics

CYP2C19 poor metabolizer status is associated with diminished response to clopidogrel. The optimal dose regimen for poor metabolizers has yet to be determined. (See CLINICAL PHARMACOLOGY: Pharmacogenetics.)

No dosage adjustment is necessary for elderly patients or patients with renal disease. (See CLINICAL PHARMACOLOGY: Special Populations.)

HOW SUPPLIED

PLAVIX (clopidogrel bisulfate) 75-mg tablets are available as pink, round, biconvex, film-coated tablets debossed with "75" on one side and "1171" on the other. Tablets are provided as follows:

NDC 63653-1171-6 bottles of 30 NDC 63653-1171-1 bottles of 90 NDC 63653-1171-5 bottles of 500 NDC 63653-1171-3 blisters of 100

PLAVIX (clopidogrel bisulfate) 300-mg tablets are available as pink, oblong, film-coated tablets debossed with "300" on one side and "1332" on the other. Tablets are provided as follows:

NDC 63653-1332-2 unit-dose packages of 30
NDC 63653-1332-3 unit-dose packages of 100

Storage

Store at 25° C (77° F); excursions permitted to 15°–30° C (59°–86° F) [See USP Controlled Room Temperature].

Distributed by:
Bristol-Myers Squibb/Sanofi Pharmaceuticals Partnership
Bridgewater, NJ 08807

PLAVIX® is a registered trademark.

Revised October 2009

Principal Display Panel - 75 mg Carton

List No. 1171-30

NDC 63653-1171-3
100 tablets

Plavix®
(clopidogrel bisulfate)

75 mg

Rx only

Information for Patients
Patients should be told that while taking PLAVIX or PLAVIX
combined with aspirin:
* it may take them longer than usual to stop bleeding;
* they may bruise and/or bleed more easily;
* they should report any unusual bleeding to their physician;
* they should tell their physician about any other medications they are
taking, including prescription or over-the-counter omeprazole;
* they should inform physicians and dentists that they are taking PLAVIX
and/or any other product known to affect bleeding before any surgery is
scheduled and before any new drug is taken.
Drug Interactions
Clopidogrel is metabolized to its active metabolite in part by
CYP2C19. Concomitant use of drugs that inhibit the activity of this enzyme
results in reduced plasma concentrations of the active metabolite of clopidogrel
and a reduction in platelet inhibition. Avoid concomitant use of drugs that
inhibit CYP2C19, including omeprazole, esomeprazole, cimetidine, fluconazole,
ketoconazole, voriconazole, etravirine, felbamate, fluoxetine, fluvoxamine, and
ticlopidine (see WARNINGS).
Studies of specific drug interactions yielded the following results:
Omeprazole
In a crossover clinical study, 72 healthy subjects were
administered PLAVIX (300-mg loading dose followed by 75 mg/day) alone and with
omeprazole (80 mg at the same time as PLAVIX) for 5 days. The exposure to the
active metabolite of clopidogrel was decreased by 46% (Day 1) and 42% (Day 5)
when PLAVIX and omeprazole were administered together. Mean inhibition of
platelet aggregation (IPA) was diminished by 47% (24 hours) and 30% (Day 5) when
PLAVIX and omeprazole were administered together. In another study 72 healthy
subjects were given the same doses of PLAVIX and omeprazole but the drugs were
administered 12 hours apart; the results were similar indicating that
administering PLAVIX and omeprazole at different times does not prevent their
interaction (see WARNINGS).
Aspirin
Aspirin did not modify the clopidogrel-mediated inhibition of
ADP-induced platelet aggregation. Concomitant administration of 500 mg of
aspirin twice a day for 1 day did not significantly increase the prolongation of
bleeding time induced by PLAVIX. PLAVIX potentiated the effect of aspirin on
collagen-induced platelet aggregation. PLAVIX and aspirin have been administered
together for up to one year.
Heparin
In a study in healthy volunteers, PLAVIX did not necessitate
modification of the heparin dose or alter the effect of heparin on coagulation.
Coadministration of heparin had no effect on inhibition of platelet aggregation
induced by PLAVIX.
Nonsteroidal Anti-Inflammatory Drugs (NSAIDs)
In healthy volunteers receiving naproxen, concomitant
administration of PLAVIX was associated with increased occult gastrointestinal
blood loss. NSAIDs and PLAVIX should be coadministered with caution.
Warfarin
Because of the increased risk of bleeding, the concomitant
administration of warfarin with PLAVIX should be undertaken with caution. (See
PRECAUTIONS: General.)
Other Concomitant Therapy
No clinically significant pharmacodynamic interactions were
observed when PLAVIX was coadministered with atenolol,
nifedipine, or both atenolol and nifedipine. The pharmacodynamic activity
of PLAVIX was also not significantly influenced by the coadministration of phenobarbital or estrogen.
The pharmacokinetics of digoxin or theophylline were not modified by the coadministration of
PLAVIX (clopidogrel bisulfate).
At high concentrations in vitro, clopidogrel
inhibits P450 (2C9). Accordingly, PLAVIX may interfere
with the metabolism of phenytoin, tamoxifen, tolbutamide,
warfarin, torsemide, fluvastatin, and many non-steroidal
anti-inflammatory agents, but there are no data with which to predict the
magnitude of these interactions. Caution should be used when any of these drugs
is coadministered with PLAVIX.
In addition to the above specific interaction studies, patients entered into
clinical trials with PLAVIX received a variety of concomitant medications
including diuretics, beta-blocking agents, angiotensin
converting enzyme inhibitors, calcium antagonists, cholesterol lowering agents,
coronary vasodilators, antidiabetic agents (including insulin), thrombolytics, heparins
(unfractionated and LMWH), GPIIb/IIIa antagonists,
antiepileptic agents and hormone replacement
therapy without evidence of clinically significant adverse
interactions.
There are no data on the concomitant use of oral anticoagulants, non study
oral anti-platelet drugs and chronic NSAIDs with clopidogrel.
Drug/Laboratory Test Interactions
None known.
Carcinogenesis, Mutagenesis, Impairment of
Fertility
There was no evidence of tumorigenicity when clopidogrel was
administered for 78 weeks to mice and 104 weeks to rats at dosages up to 77
mg/kg per day, which afforded plasma exposures >25 times that in humans at
the recommended daily dose of 75 mg.
Clopidogrel was not genotoxic in four in vitro
tests (Ames test, DNA-repair test in rat hepatocytes, gene mutation assay in
Chinese hamster fibroblasts, and metaphase chromosome analysis of human
lymphocytes) and in one in vivo test (micronucleus
test by oral route in mice).
Clopidogrel was found to have no effect on fertility of male and female rats
at oral doses up to 400 mg/kg per day (52 times the recommended human dose on a
mg/m2 basis).
Pregnancy Pregnancy Category B
Reproduction studies performed in rats and rabbits at doses up to
500 and 300 mg/kg/day (respectively, 65 and 78 times the recommended daily human
dose on a mg/m2 basis), revealed no evidence of impaired
fertility or fetotoxicity due to clopidogrel. There are, however, no adequate
and well-controlled studies in pregnant women. Because animal reproduction
studies are not always predictive of a human response, PLAVIX should be used
during pregnancy only if clearly needed.
Nursing Mothers
Studies in rats have shown that clopidogrel and/or its
metabolites are excreted in the milk. It is not known whether this drug is
excreted in human milk. Because many drugs are excreted in human milk and
because of the potential for serious adverse reactions in nursing infants, a
decision should be made whether to discontinue nursing or to discontinue the
drug, taking into account the importance of the drug to the nursing woman.
Pediatric Use
Safety and effectiveness in the pediatric population have not
been established.
Geriatric Use
Of the total number of subjects in the CAPRIE, CURE and CLARITY
controlled clinical studies, approximately 50% of patients treated with PLAVIX
were 65 years of age and older, and 15% were 75 years and older. In COMMIT,
approximately 58% of the patients treated with PLAVIX were 60 years and older,
26% of whom were 70 years and older.
The observed risk of thrombotic events with clopidogrel plus aspirin versus
placebo plus aspirin by age category is provided in Figures 3 and 6 for the CURE
and COMMIT trials, respectively (see CLINICAL
STUDIES). The observed risk of bleeding events with clopidogrel plus
aspirin versus placebo plus aspirin by age category is provided in Tables 6 and
7 for the CURE and COMMIT trials, respectively (see ADVERSE REACTIONS).

LABEL IMAGE